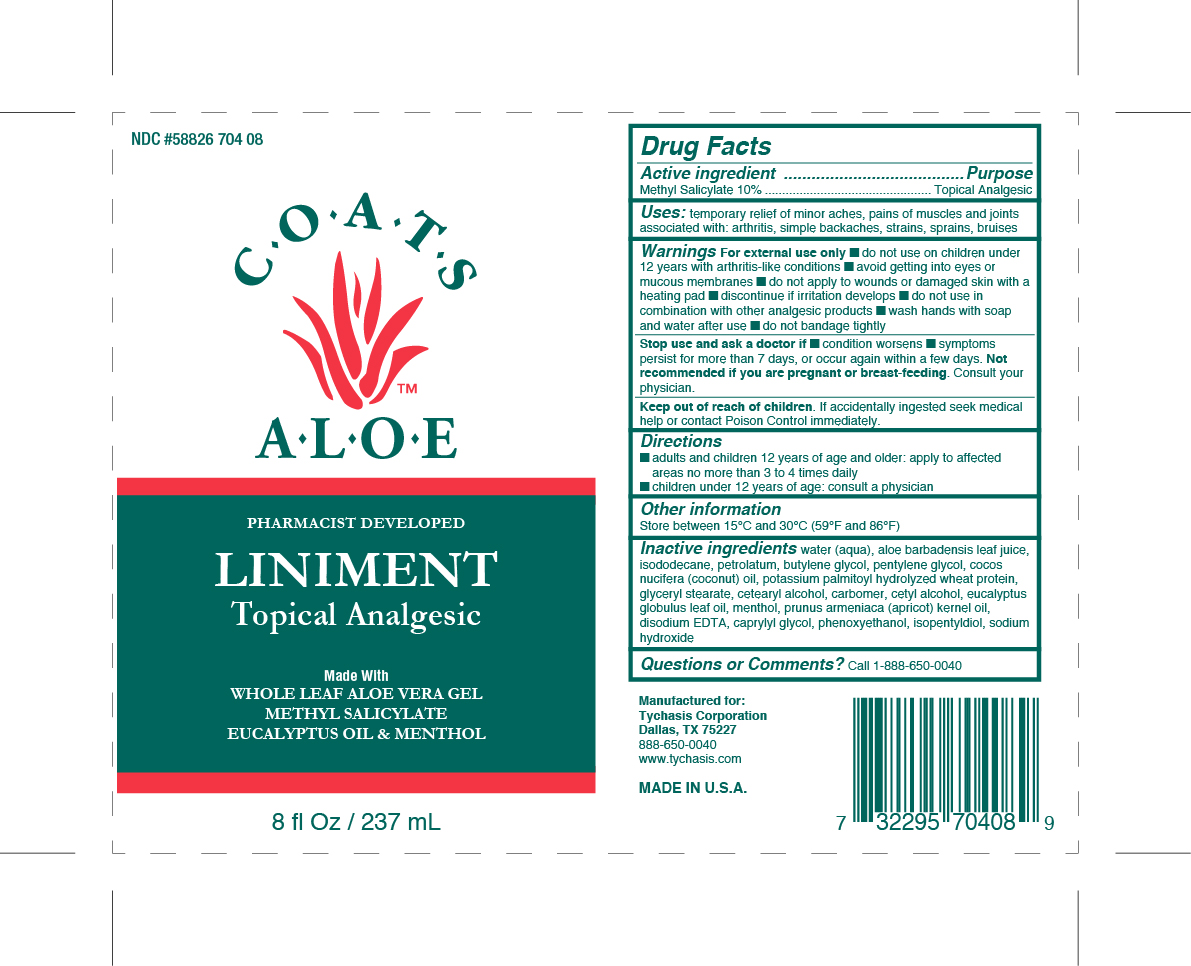 DRUG LABEL: COATS ALOE ANALGESIC
NDC: 58826-704 | Form: LOTION
Manufacturer: TYCHASIS CORPORATION
Category: otc | Type: HUMAN OTC DRUG LABEL
Date: 20151005

ACTIVE INGREDIENTS: METHYL SALICYLATE 10 g/1 g
INACTIVE INGREDIENTS: PETROLATUM; ISODODECANE; ISOPENTYLDIOL; PENTYLENE GLYCOL; PHENOXYETHANOL; CETYL ALCOHOL; EUCALYPTUS GLOBULUS LEAF; HYDROLYZED WHEAT PROTEIN (ENZYMATIC, 3000 MW); PRUNUS ARMENIACA SEED; SODIUM HYDROXIDE; WATER; COCOS NUCIFERA WHOLE; BUTYLENE GLYCOL; CAPRYLYL GLYCOL; MENTHOL; ALOE VERA WHOLE

COATS ALOE LINIMENT

ACTIVE INGREDIENT

METHYL SALICYLATE 10% TOPICAL ANALGESIC

MENTHOL 1%

USE

TEMPORARY RELIEF OF MINOR ACHES AND PAINS OF MUSCLES AND JOINTS ASSOCIATED WITH: ARTHRITIS, SIMPLE BACKACHES, STRAINS, SPRAINS, BRUISES

PURPOSE

Topical analgesic, topical pain relief for intact skin

WARNINGS

FOR EXTERNAL USE ONLY

AVOID CONTACT WITH EYES OR MUCOUS MEMBRANES

DO NOT APPLY TO WOUNDS OR DAMAGED SKIN WITH A HEATING PAD

DISCONTINUE IF IRRITATION DEVELOPS

DO NOT USE IN COMBINATION WITH OTHER ANALGESIC PRODUCTS

WASH HANDS WITH SOAP AND WATER AFTER USE

DO NOT BANDAGE TIGHTLY

STOP USE AND ASK DOCTOR IF CONDITION WORSENS IF SYMPTOMS PERSIST MORE THAN 7 DAYS, OR IF SYMPTOMS WORSEN WITHIN A FEW DAYS.

NOT RECOMMENDED IF YOU ARE PREGNANT OR BREASTFEEDING. CONSULT YOUR PHYSICIAN.

KEEP OUT OF REACH OF CHILDREN. IF ACCIDENTALLY INGESTED SEEK MEDICAL HELP OR CONTACT POISON CONTROL IMMEDIATELY.

DIRECTIONS

ADULTS AND CHILDREN 12 YEARS OF AGE AND OLDER: apply to affected areas no more than 3-4 times daily.

CHILDREN UNDER 12 YEARS OF AGE: consult a physician.

OTHER INFORMATION

STORE BETWEEN 15^0C AND 30^0C (59^0F AND 86^0F)

INACTIVE INGREDIENTS

Aloe Barbadenesis Leaf Juice, Butylene Glycol, Caprylyl Glycol, Carbomer, Cetearyl Alcohol, Cetyl Alcohol, Cocos Nucifera (Coconut) Oil, Disodium EDTA, Eucalyptus Globulus Leaf Oil, Glyceryl Stearate, Isododecane, Isopentylidiol, Menthol, Pentylene Glycol, Petrolatum, Phenoxyethanol, Potassium palmitol hyrdrolyzed wheat protein, Prunus Armeniaca (Apricot Kernel Oil), Sodium Hyrdroxide, Water (Aqua)

Keep out of reach of children. If accidentally ingested seek medical help or contact Poison Control immediately.

QUESTIONS

888-650-0040

customerservice@coatsaloevera.com